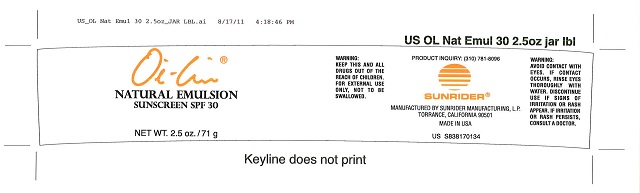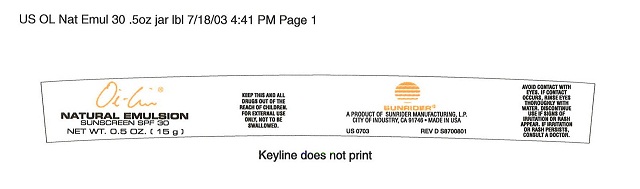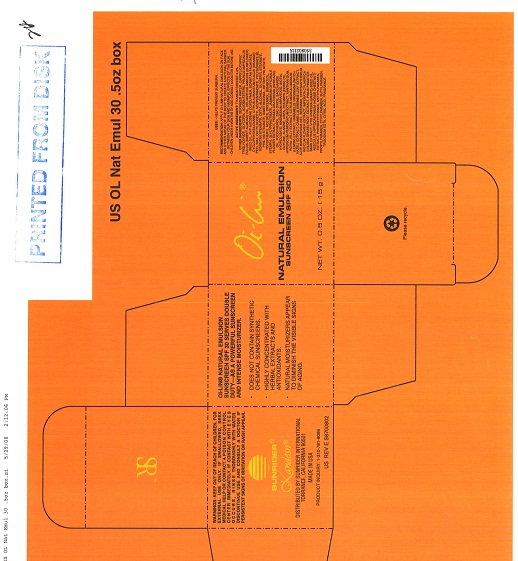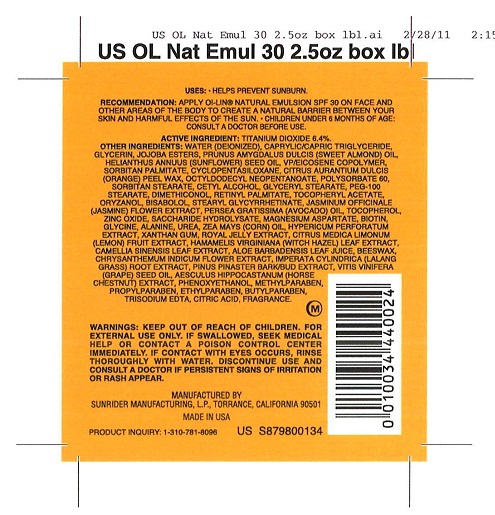 DRUG LABEL: Oi Lin Natural Sunscreen SPF 30
NDC: 62191-004 | Form: EMULSION
Manufacturer: Sunrider Manufacturing L.P.
Category: otc | Type: HUMAN OTC DRUG LABEL
Date: 20120206

ACTIVE INGREDIENTS: TITANIUM DIOXIDE 0.66 g/1 g
INACTIVE INGREDIENTS: ALANINE; ALOE VERA LEAF; YELLOW WAX; Biotin; BUTYLPARABEN; Cetyl Alcohol; CYCLOMETHICONE 5; DENDRANTHEMA INDICUM FLOWER; ETHYLPARABEN; GAMMA ORYZANOL; Glycerin; GLYCERYL MONOSTEARATE; GREEN TEA LEAF; HAMAMELIS VIRGINIANA TOP; HORSE CHESTNUT; HYPERICUM PERFORATUM FLOWER; IMPERATA CYLINDRICA ROOT; MAGNESIUM ASPARTATE; MEDIUM-CHAIN TRIGLYCERIDES; METHYLPARABEN; OCTYLDODECYL NEOPENTANOATE; ORANGE PEEL WAX; PEG-100 STEARATE; SUNFLOWER OIL; WATER

OIL LIN® NATURAL EMULSION SUNSCREEN SPF 30

PURPOSE

USES: HELPS PREVENT SUNBURN

INDICATIONS AND USAGE

RECOMMENDATION: APPLY OI-LIN® NATURAL EMULSION SPF 30 ON FACE AND OTHER AREAS OF THE BODY TO CREATE A NATURAL BARRIER BETWEEN YOUR SKIN AND HARMFUL EFFECTS OF THE SUN. CHILDREN UNDER 6 MONTHS OF AGE; CONSULT A PHYSICIAN BEFORE USE.

ACTIVE INGREDIENT: TITANIUM DIOXIDE 6.4%

INACTIVE INGREDIENT

OTHER INGREDIENTS: WATER (DEIONIZED), CAPRYLIC/CAPRIC TRIGLYCERIDE, GLYCERIN, JOJOBA ESTERS, PRUNUS AMYGDALUS DULCIS (SWEET ALMOND) OIL, HELIANTHUS ANNUUS (SUNFLOWER) SEED OIL, VP/EICOSENE COPOLYMER, SORBITAN PALMITATE, CYCLOPENTASILOXANE, CITRUS AURANTIUM DULCIS (ORANGE) PEEL WAX, OCTYLDODECYL, NEOPENTANOATE, POLYSORBATE 60, SORBITAN STEARATE, CETYL ALCOHOL, GLYCERYL STEARATE, PEG-100 STEARATE, DEMETHICONOL, RETINYL PALMITATE, TOCOPHERYL ACETATE, ORYZANOL, BISABOLOL, STEARYL GLYCYRRHETINATE, JASMINUM OFFICINALE, (JASMINE0 FLOWER EXTRACT, PERSEA GRATISSIMA (AVOCATO) OIL, TOCOPHEROL, ZINC OXIDE, SACCHARIDE HYDROLYSATE, MAGNESIUM ASPARTATE, BIOTIN, GLYCINE, ALANINE, UREA, ZEA MAYS (CORN) OIL, HYPERICUM PERFORATUM EXTRACT, XANTHAN GUM, ROYAL JELLY EXTRACT, CITRUS MEDICA LIMONUM (LEMON) FRUIT EXTRACT, HAMAMELIS VIRGINIANA (WITCH HAZEL) LEAF EXTRACT, CAMELLIA SINENSIS LEAF EXTRACT, ALOE BARBADENSIS LEAF JUICE, BEESWAX, CHRYSANTHEMUM INDICUM FLOWER EXTRACT, IMPERATA CYLINDRICA (LALANG GRASS) ROOT EXTRACT, PINUS PINASTER BARK/BUD EXTRACT, VITIS VINIFERA (GRAPE) SEED OIL, AESCULUS HIPPOCASTANUM (HORSE CHESTNUT) EXTRACT, PHENOXYETHANOL, METHYLPARABEN, PROPYLPARABEN, ETHYLPARABEN, BUTYLPARABEN, TRISODIUM EDTA, CITRIC ACID, FRAGRANCE.

WARNINGS

WARNING:FOR EXTERNAL USE ONLY. IF SWALLOWED, SEEK MEDICAL HELP OR CONTACT A POISON CONTROL CENTER IMMEDIATELY, IF CONTACT WITH EYES OCCURS, RINSE THOROUGHLY WITH WATER. DISCONTINUE USE AND CONSULT A PHYSICIAN IF PERSISTENT SIGNS OF IRRITATION OR RASH APPEAR.

KEEP OUT OF REACH OF CHILDREN

PACKAGE LABEL

MM1
MM2
MM3
MM4
USES: HELPS PREVENT SUNBURNS